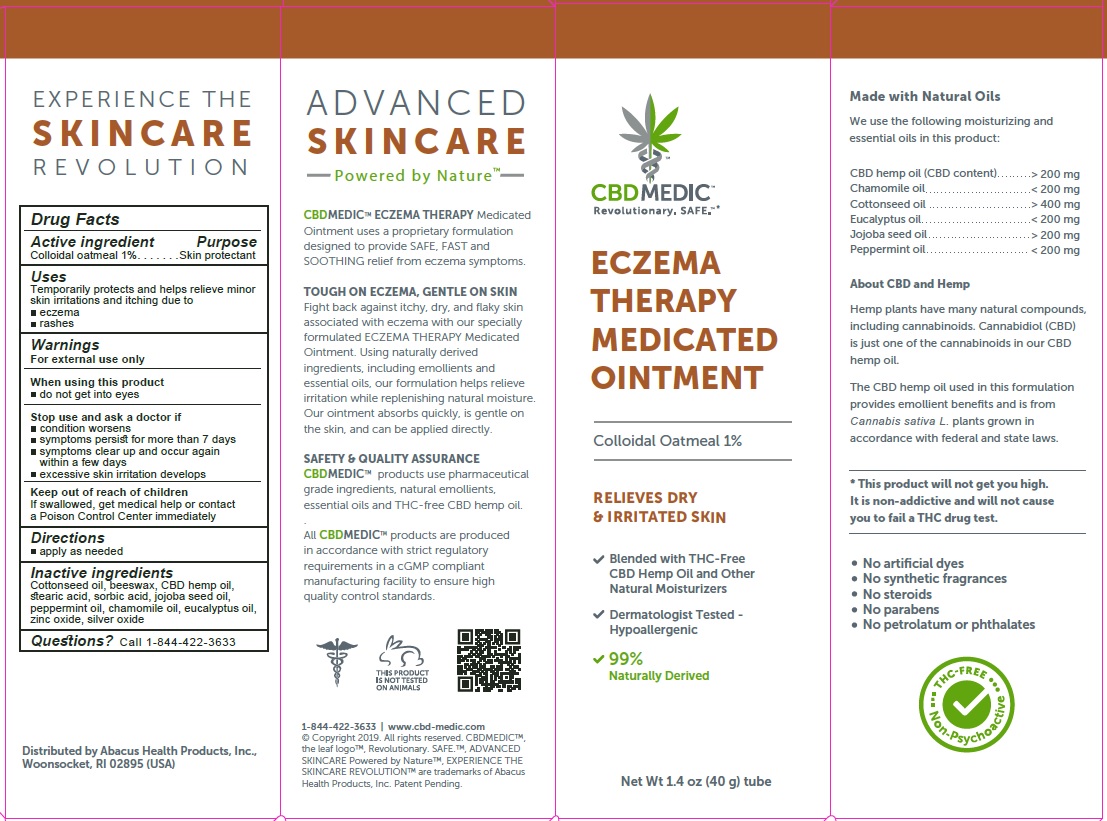 DRUG LABEL: CBDMEDIC Eczema Therapy
NDC: 24909-751 | Form: OINTMENT
Manufacturer: AIDANCE SKINCARE & TOPICAL SOLUTIONS, LLC
Category: otc | Type: HUMAN OTC DRUG LABEL
Date: 20191225

ACTIVE INGREDIENTS: OATMEAL 10 mg/1 g
INACTIVE INGREDIENTS: WHITE WAX; CHAMAEMELUM NOBILE FLOWER OIL; COTTONSEED OIL; EUCALYPTUS OIL; HEMP; JOJOBA OIL; PEPPERMINT OIL; SILVER OXIDE; SORBIC ACID; STEARIC ACID; ZINC OXIDE

CBDMEDIC Eczema Therapy

Active Ingredients and Purpose

Colloidal Oatmeal 1% (Skin Protectant)

Uses

Temporarily protects and helps relieve minor skin irritations and itching due to
• eczema
• rashes

Warnings

For external use only
When using this product
• do not get into eyes
Stop use and ask a doctor if
• condition worsens
• symptoms persist for more than 7 days
• symptoms clear up and occur again within a few days
• excessive skin irritation develops
Keep out of reach of children
If swallowed, get medical help or contact a Poison Control Center immediately

Directions

apply as needed

Inactive ingredients

Cottonseed oil, beeswax, CBD hemp oil, stearic acid, sorbic acid, jojoba seed oil, peppermint oil, chamomile oil, eucalyptus oil, zinc oxide, silver oxide

Questions?

Call 1-844-422-3633